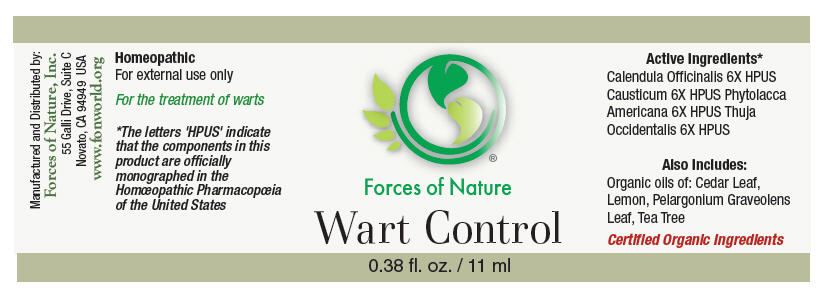 DRUG LABEL: Wart Control
NDC: 51393-7333 | Form: SOLUTION/ DROPS
Manufacturer: Forces of Nature
Category: homeopathic | Type: HUMAN OTC DRUG LABEL
Date: 20100824

ACTIVE INGREDIENTS: CALENDULA OFFICINALIS FLOWERING TOP 6 [hp_X]/1000 mL; Causticum 6 [hp_X]/1000 mL; Phytolacca Americana Root 6 [hp_X]/1000 mL; Thuja occidentalis leafy twig 6 [hp_X]/1000 mL

Wart Control

Drug Facts

Indications

For the treatment of warts.

ACTIVE INGREDIENT

PURPOSE

Homeopathic Active Ingredients [The letters 'HPUS' indicate that the components in this product are officially monographed in the Homœopathic Pharmacopœia of the United States.]
Equal parts of: | Purpose
Calendula Officinalis 6X HPUS | promotes healthy skin
Causticum 6X HPUS | for healing of warts
Phytolacca Americana 6X HPUS | heals skin tags, moles and warts
Thuja Occidentalis 6X HPUS | heals skin eruptions, polyps, warts nevi (moles)

Also Contains Certified Organic

Cedar Leaf Oil, Lemon Oil, Pelargonium Graveolens Leaf Oil, Tea Tree Oil

Directions

Moisten a cotton swab (or Q-tip) with a few drops, dab moistened swab directly to warts 3 times each day. If possible, secure a band-aid over the wart/s after applying treatment. It is important to note that an apparent increase in the size of the wart often signals the beginning of the healing process. Those parts of the wart hidden beneath the skin are rejected by the healing tissue and are pushed outward. Warts usually flake away after 2-5 weeks of treatment when these directions are followed. Cluster warts may take longer to treat before desired results are achieved. If you experience irritation from use, wash area with warm soapy water before further applications and apply less product. If irritation continues, discontinue use. It is recommended to wash the area with warm soapy water before each application.

Warnings

ASK DOCTOR

This product does not prevent the spread of warts. If problem persists, see your doctor.

STOP USE

Some individuals may be sensitive to tea tree or other oils. Begin with a small drop to determine if the product causes any increased redness or irritation and discontinue use if it irritates your skin.

PREGNANCY OR BREAST FEEDING

If you are pregnant or breast-feeding, ask a health professional before use.

Do not use this product on irritated skin.

KEEP OUT OF REACH OF CHILDREN

Keep out of the reach of children. If accidental ingestion, get medical help or contact a Poison Control Center. For external use only. Do not apply to the eyes. Keep all medicines out of the reach of children.

Manufactured by:
Forces of Nature, Inc.
55 Galli Drive, Suite C
Novato, CA 94949 USA
www.fonworld.org

Product questions?

877-975-3797

NDC #: 51393-7333-1 (11ml) // 51393-7333-2 (33ml)

PRINCIPAL DISPLAY PANEL - 11 ml Bottle Label

Forces of Nature

Wart Control

0.38 fl. oz. / 11 ml